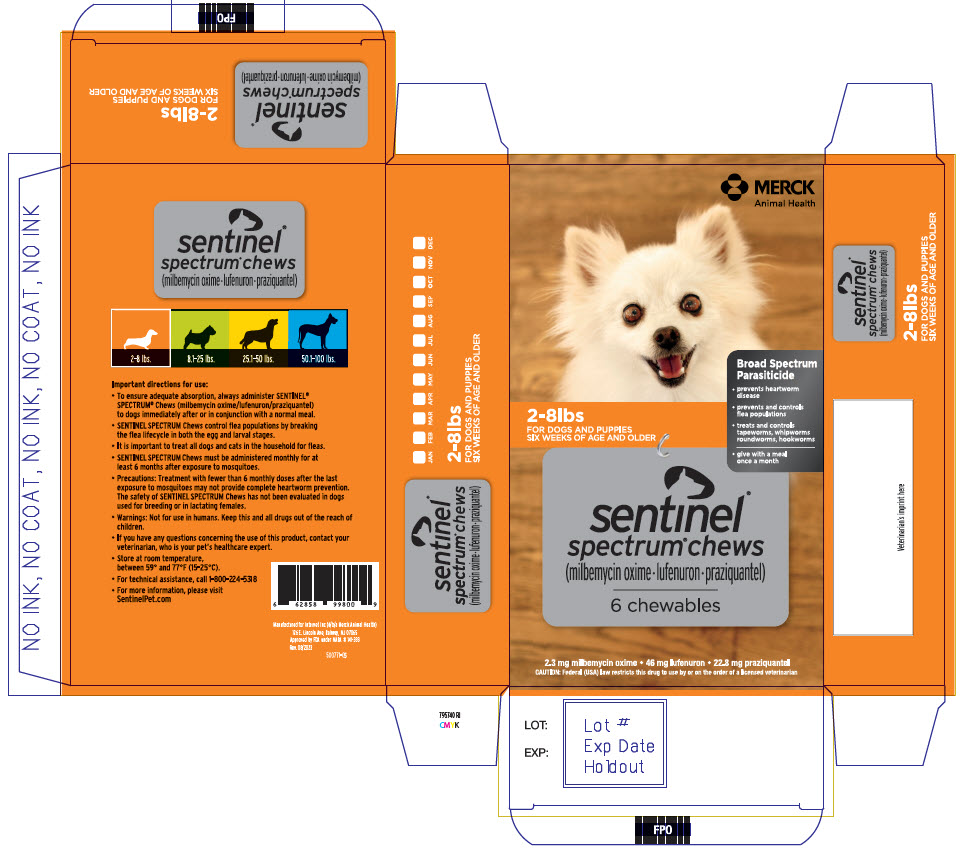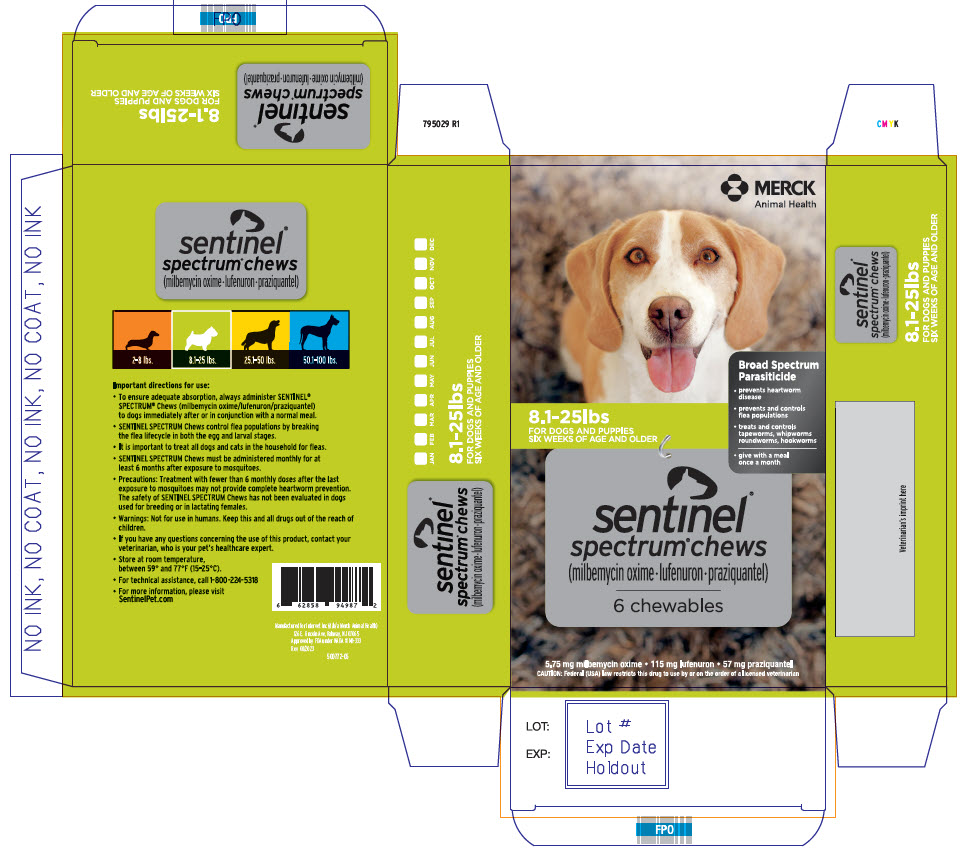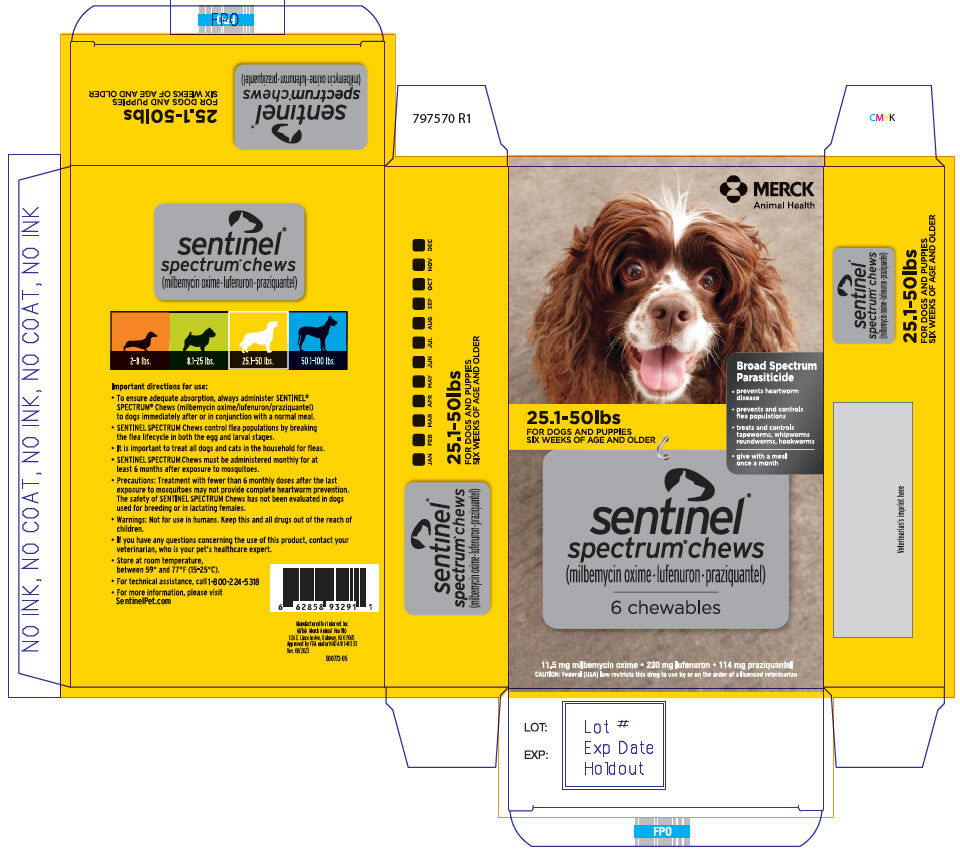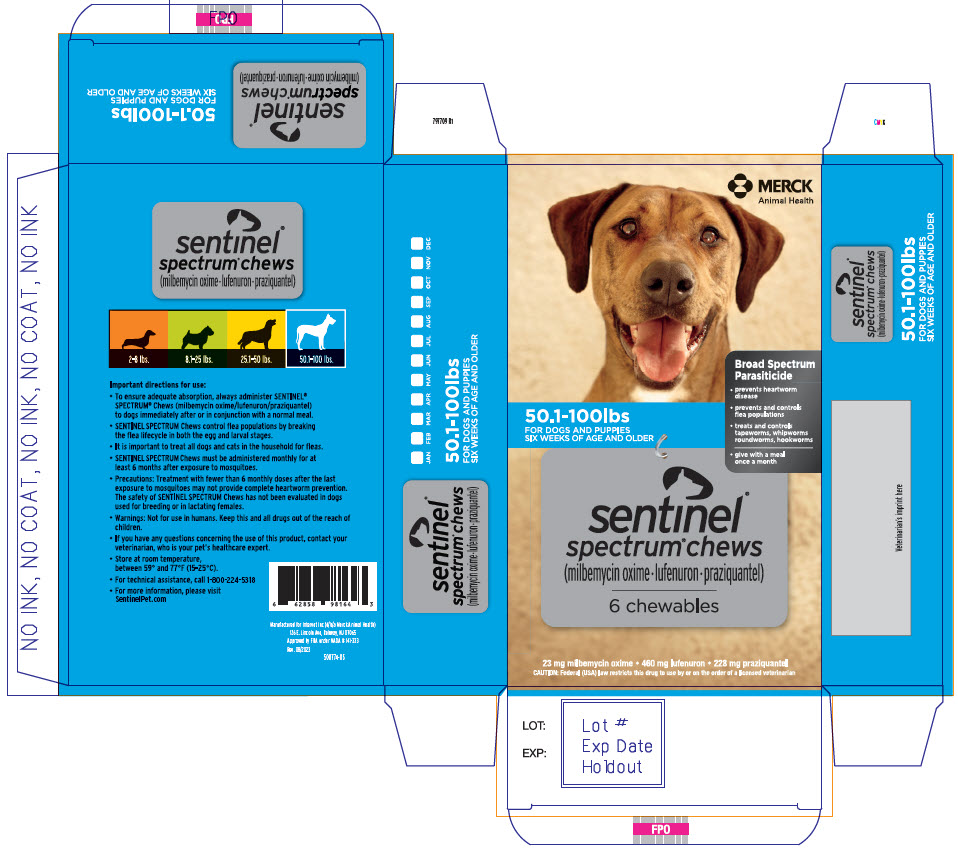 DRUG LABEL: Sentinel Spectrum
NDC: 0061-5354 | Form: TABLET, CHEWABLE
Manufacturer: Merck Sharp & Dohme Corp.
Category: animal | Type: PRESCRIPTION ANIMAL DRUG LABEL
Date: 20250925

ACTIVE INGREDIENTS: MILBEMYCIN OXIME 2.3 mg/1 1; LUFENURON 46 mg/1 1; PRAZIQUANTEL 22.8 mg/1 1

sentinel®
spectrum® chews
(milbemycin oxime • lufenuron • praziquantel)

MERCK
Animal Health

WARNINGS

Caution: Federal (USA) law restricts this drug to use by or on the order of a licensed veterinarian.

DESCRIPTION

Description: SENTINEL® SPECTRUM® Chews are available in four strengths in color-coded packages for oral administration to dogs and puppies according to their weight. Each chewable flavored tablet is formulated to provide a minimum of 0.23 mg/pound (0.5mg/kg) of milbemycin oxime, 4.55 mg/pound (10mg/kg) of lufenuron, and 2.28 mg/pound (5mg/kg) of praziquantel.

Milbemycin oxime consists of the oxime derivatives of 5-didehydromilbemycins in the ratio of approximately 80% A4 (C32H45NO7, MW 555.71) and 20% A3 (C31H43NO7, MW 541.68). Milbemycin oxime is classified as a macrocyclic anthelmintic.

Lufenuron is a benzoylphenylurea derivative with the following chemical composition: N-[[[2,5-Dichloro-4-(1,1,2,3,3,3-hexafluoropropoxy)phenyl]amino]carbonyl]-2,6-difluorobenzamide (C17H8CI2F8N2O3, MW 511.15). Benzoylphenylurea compounds, including lufenuron, are classified as insect development inhibitors (IDIs).

Praziquantel is an isoquinolone anthelmintic with the chemical name 2-(Cyclohexylcarbonyl)-1,2,3,6,7,-11b-hexahydro-4H-pyrazino[2,1-a]isoquinolin-4-one.

INDICATIONS AND USAGE

Indications: SENTINEL SPECTRUM Chews are indicated for the prevention of heartworm disease caused by Dirofilaria immitis; for the prevention and control of flea populations (Ctenocephalides felis); and for the treatment and control of adult roundworm (Toxocara canis, Toxascaris leonina), adult hookworm (Ancylostoma caninum), adult whipworm (Trichuris vulpis), and adult tapeworm (Dipylidium caninum, Taenia pisiformis, Echinococcus multilocularis and Echinococcus granulosus) infections in dogs and puppies two pounds of body weight or greater and six weeks of age and older.

Dosage and Administration: SENTINEL SPECTRUM Chews should be administerd orally, once every month, at the minimum dosage of 0.23 mg/lb (0.5 mg/kg) milbemycin oxime, 4.55 mg/lb (10 mg/kg) lufenuron, and 2.28 mg/lb (5 mg/kg) praziquantel. For heartworm prevention, give once monthly for at least 6 months after exposure to mosquitoes (see EFFECTIVENESS).

Dosage Schedule
Body Weight | Milbemycin Oxime per chewable | Lufenuron per chewable | Praziquantel per chewable | Number of chewables
2 to 8 lbs. | 2.3 mg | 46 mg | 22.8 mg | One
8.1 to 25 lbs. | 5.75 mg | 115 mg | 57 mg | One
25.1 to 50 lbs. | 11.5 mg | 230 mg | 114 mg | One
50.1 to 100 lbs. | 23.0 mg | 460 mg | 228 mg | One
Over 100 lbs. | Administer the appropriate combination of chewables

To ensure adequate absorption, always administer SENTINEL SPECTRUM Chews to dogs immediately after or in conjunction with a normal meal.

SENTINEL SPECTRUM Chews may be offered to the dog by hand or added to a small amount of dog food. The chewables should be administered in a manner that encourages the dog to chew, rather than to swallow without chewing. Chewables may be broken into pieces and fed to dogs that normally swallow treats whole. Care should be taken that the dog consumes the complete dose, and treated animals should be observed a few minutes after administration to ensure that no part of the dose is lost or rejected. If it is suspected that any of the dose has been lost, redosing is recommended.

Heartworm Prevention: SENTINEL SPECTRUM Chews should be administered at monthly intervals beginning within one month of the dog's first seasonal exposure to mosquitoes and continuing until at least 6 months after the dog's last seasonal exposure (see EFFECTIVENESS). SENTINEL SPECTRUM Chews may be administered year-round without interruption. When switching from another heartworm preventative product to SENTINEL SPECTRUM Chews, the first dose of SENTINEL SPECTRUM Chews should be given within a month of the last dose of the former product.

Flea Treatment and Prevention: Treatment with SENTINEL SPECTRUM Chews may begin at any time of the year, preferably starting one month before fleas become active and continuing monthly through the end of flea season. In areas where fleas are common year-round, monthly treatment with SENTINEL SPECTRUM Chews should continue the entire year without interruption.

To minimize the likelihood of flea reinfestation, it is important to treat all animals within a household with an approved flea protection product, as necessary.

Intestinal Nematode and Cestode Treatment and Control: Dogs may be exposed to and can become infected with roundworms, whipworms, hookworms, and tapeworms throughout the year, regardless of season or climate. Clients should be advised of appropriate measures to prevent reinfection of their dog with intestinal parasites. Because the prepatent period for E. multilocularis may be as short as 26 days, dogs treated at the labeled monthly intervals may become reinfected and shed eggs between treatments.

CONTRAINDICATIONS

Contraindications: There are no known contraindications to the use of SENTINEL SPECTRUM Chews.

WARNINGS

Warnings: Not for use in humans. Keep this and all drugs out of the reach of children.

PRECAUTIONS

Precautions: Treatment with fewer than 6 monthly doses after the last exposure to mosquitoes may not provide complete heartworm prevention (see EFFECTIVENESS).

Prior to administration of SENTINEL SPECTRUM Chews, dogs should be tested for existing heartworm infections. At the discretion of the veterinarian, infected dogs should be treated to remove adult heartworms. SENTINEL SPECTRUM Chews are not effective against adult D. immitis.

Mild, transient hypersensitivity reactions, such as labored breathing, vomiting, hypersalivation, and lethargy have been noted in some dogs treated with milbemycin oxime carrying a high number of circulating microfilariae. These reactions are presumably caused by release of protein from dead or dying microfilariae.

Do not use in puppies less than six weeks of age.

Do not use in dogs or puppies less than two pounds of body weight.

The safety of SENTINEL® SPECTRUM® Chews has not been evaluated in dogs used for breeding or in lactating females. Studies have been performed with milbemycin oxime and lufenuron alone (see ANIMAL SAFETY).

ADVERSE REACTIONS

Adverse Reactions: The following adverse reactions have been reported in dogs after administration of milbemycin oxime, lufenuron, or praziquantel: vomiting, depression/lethargy, pruritus, urticaria, diarrhea, anorexia, skin congestion, ataxia, convulsions, salivation, and weakness.

To report suspected adverse drug events, contact Merck Animal Health at 1-800-224-5318. For additional information about adverse drug experience reporting for animal drugs, contact FDA at 1-888-FDA-VETS or http://www.fda.gov/reportanimalae.

For technical assistance, call Merck Animal Health at 1-800-224-5318.

Information for Owner or Person Treating Animal: Echinococcus multilocularis and Echinococcus granulosus are tapeworms found in wild canids and domestic dogs. E. multilocularis and E. granulosus can infect humans and cause serious disease (alveolar hydatid disease and hydatid disease, respectively). Owners of dogs living in areas where E. multilocularis or E. granulosus are endemic should be instructed on how to minimize their risk of exposure to these parasites, as well as their dog's risk of exposure. Although SENTINEL SPECTRUM Chews were 100% effective in laboratory studies in dogs against E. multilocularis and E. granulosus, no studies have been conducted to show that the use of this product will decrease the incidence of alveolar hydatid disease or hydatid disease in humans. Because the prepatent period for E. multilocularis may be as short as 26 days, dogs treated at the labeled monthly intervals may become reinfected and shed eggs between treatments.

Effectiveness

Heartworm Prevention: In a well-controlled laboratory study, SENTINEL SPECTRUM Chews (milbemycin oxime, lufenuron, praziquantel) were 100% effective against induced heartworm infections when administered once monthly for 6 consecutive months. In well-controlled laboratory studies, neither one dose nor two consecutive doses of SENTINEL SPECTRUM Chews provided 100% effectiveness against induced heartworm infections.

Intestinal Nematodes and Cestodes Treatment and Control: Elimination of the adult stage of hookworm (Ancylostoma caninum), roundworm (Toxacara canis, Toxascaris leonina), whipworm (Trichuris vulpis) and tapeworm (Dipylidium caninum, Echinococcus multilocularis, Echinococcus granulosus, Taenia pisiformis) infections in dogs was demonstrated in well-controlled laboratory studies.

Flea Prevention and Control: In well-controlled studies, SENTINEL SPECTRUM Chews were effective in preventing flea eggs from hatching, thus providing control of the development of flea populations (Ctenocephalides felis).

Palatability: In a field study of 117 dogs offered SENTINEL SPECTRUM Chews, 113 dogs (96.6%) accepted the product when offered from the hand as if a treat, 2 dogs (1.7%) accepted it from the bowl with food, 1 dog (0.9%) accepted it when it was placed in the dog's mouth, and 1 dog (0.9%) refused it.

Animal Safety: In a margin of safety study, 40 ten-week-old puppies (10 per group) were administered either a sham dose (0X) or doses of 1, 3, or 5X the maximum exposure dose of SENTINEL SPECTRUM Chews once every two weeks for a total of seven treatments. Transient ataxia, lethargy, tremors, and salivation were seen in the 3X and 5X groups following each of the seven doses. Lethargy and ataxia were occasionally reported in sham-dosed (0X) and 1X dogs. Tremors were observed twice post-treatment in the 1X treatment group. Vomiting was seen in all treatment groups but at a higher incidence in the 3X and 5X groups. At the 5X dose, shallow breathing was noted in two dogs and one dog was unable to stand following two different doses. All clinical signs resolved within 24 hours.

In a second margin of safety study, 64 six-week-old puppies (16 per group) were dosed with either a sham (0X) or 1, 3, or 5X the maximum exposure dose of SENTINEL SPECTRUM Chews on days 1, 15, 29, and 43. A dose dependent increase in ataxia, decreased activity, tremors, and salivation was seen within 24 hours of treatment. Splayed hind limbs were observed once in one dog in the 5X treatment group. Vomiting was observed in the 5X treatment group.

For SENTINEL SPECTRUM Chews, the maximum exposure based on product dosing is 2.5 mg/kg for milbemycin oxime, 50.7 mg/kg for lufenuron and 25.1 mg/kg for praziquantel, which is higher than the minimum effective dose used in the safety studies for milbemycin oxime and lufenuron (see below).

Milbemycin Oxime: Two studies were conducted in heartworm-infected dogs treated with milbemycin oxime. Mild, transient hypersensitivity reactions were observed in dogs with high microfilariae counts (see PRECAUTIONS).

Safety studies in pregnant dogs demonstrated that doses of 0.6X the maximum exposure dose of SENTINEL SPECTRUM Chews, (1.5 mg/kg of milbemycin oxime), administered daily from mating through weaning, resulted in measurable concentrations of milbemycin oxime in milk. Puppies nursing these females demonstrated milbemycin oxime-related effects (depression, decreased activity, diarrhea, dehydration, nasal discharge). A subsequent study, which evaluated the daily administration of 0.6X the maximum exposure dose of SENTINEL SPECTRUM Chews, from mating until one week before weaning, demonstrated no effects on the pregnant females or their litters. A study, in which pregnant females were dosed once, at 0.6X maximum exposure dose of SENTINEL SPECTRUM Chews before, on the day of, or shortly after whelping, resulted in no effects on the puppies.

Some nursing puppies, at 2, 4, and 6 weeks of age, administered oral doses of 9.6 mg/kg milbemycin oxime (3.8X the maximum exposure dose of SENTINEL SPECTRUM Chews) exhibited tremors, vocalization, and ataxia. These effects were all transient and puppies returned to normal within 24 to 48 hours. No effects were observed in puppies administered 0.5 mg/kg milbemycin oxime (minimum label dose).

A rising-dose safety study conducted in rough-coated Collies resulted in ataxia, pyrexia, and periodic recumbency in one of fourteen dogs administered milbemycin oxime at 12.5 mg/kg (5X the maximum exposure dose of SENTINEL SPECTRUM Chews). Prior to receiving the 12.5 mg/kg dose on day 56 of the study, all animals had undergone a dosing regimen consisting of 2.5 mg/kg milbemycin oxime on day 0, followed by 5.0 mg/kg on day 14, and 10.0 mg/kg on day 32. No adverse reactions were observed in any of the Collies treated with doses less than 12.5 mg/kg.

Lufenuron: In a ten-month study, doses of lufenuron up to 2X the maximum exposure dose of SENTINEL SPECTRUM Chews (10 mg/kg) caused no overt toxicity. A single dose of 200 mg/kg had no marked effect on adult dogs, but caused decreased activity and reduced appetite in eight-week-old puppies. Lufenuron tablets were evaluated with concurrent administration of flea adulticides containing carbaryl, permethrin, chlorpyriphos, and cythioate. No toxicty resulted from these combinations. Lufenuron tablets did not cause cholinesterase inhibition nor did they enhance cholinesterase inhibition caused by exposure to organophoshphates.

Two laboratory and two well-controlled field studies were conducted to evaluate reproductive safety of lufenuron tablets in breeding dogs. In one of the laboratory studies, in which lufenuron was administered to Beagle dogs as three divided doses, equivalent to 17.8X the maximum exposure dose of SENTINEL SPECTRUM Chews (10 mg/kg), the ratio of gravid females to females mated was 8/8 or 100% in the control group and 6/9 or 67% in the lufenuron-treated group. The mean number of pups per litter was two animals higher in the lufenuron versus control groups and mean birth weights of pups from treated females in this study was lower than control groups. These pups grew at a similar rate to the control pups. The incidence of nasal discharge, pulmonary congestion, diarrhea/dehydration, and sluggishness was higher in the lufenuron-treated pup group than in the control pup group. The incidence of these signs was transient and decreasing by the end of lactation.

Results from three additional reproductive safety studies, one laboratory and two field studies, evaluating eleven breeds of dogs, did not demonstrate any adverse findings for the reproductive parameters measured, including fertility, pup birth weights, and pup clinical signs, after administration of lufenuron up to 1X the maximum exposure dose of SENTINEL SPECTRUM Chews. The average milk: blood concentration ratio was approximately 60 (i.e. 60X higher drug concentrations in the milk compared to drug levels in the blood of treated females). Nursing puppies averaged 8-9 times higher blood concentrations of lufenuron compared to their dams.

STORAGE AND HANDLING

Storage Information: Store in a dry place at controlled room temperature, between 59° and 77°F (15-25°C).

HOW SUPPLIED

How Supplied: SENTINEL SPECTRUM Chews are available in four strengths, formulated according to the weight of the dog. Each strength is available in color-coded packages of six chewable tablets each.

Manufactured for: Intervet Inc (d/b/a Merck Animal Health)
126 E. Lincoln Ave
Rahway, NJ 07065
Approved by FDA under NADA # 141-333

© 2018, 2023 Merck & Co., Inc., Rahway, NJ, USA and its affiliates. All rights reserved

Rev. 08/23
302219 - 05
799275 R1

PRINCIPAL DISPLAY PANEL - 6 Chewable Blister Pack Carton - 2-8lbs

MERCK
Animal Health

2-8lbs
FOR DOGS AND PUPPIES
SIX WEEKS OF AGE AND OLDER

Broad Spectrum
Parasiticide

- prevents heartworm
  disease
- prevents and controls
  flea populations
- treats and controls
  tapeworms, whipworms
  roundworms, hookworms
- give with a meal
  once a month

sentinel®
spectrum® chews
(milbemycin oxime • lufenuron • praziquantel)

6 chewables

2.3 mg milbemycin oxime • 46 mg lufenuron • 22.8 mg praziquantel
CAUTION: Federal (USA) law restricts this drug to use by or on the order of a licensed veterinarian

PRINCIPAL DISPLAY PANEL - 6 Chewable Blister Pack Carton - 8.1-25lbs

MERCK
Animal Health

8.1-25lbs
FOR DOGS AND PUPPIES
SIX WEEKS OF AGE AND OLDER

Broad Spectrum
Parasiticide

- prevents heartworm
  disease
- prevents and controls
  flea populations
- treats and controls
  tapeworms, whipworms
  roundworms, hookworms
- give with a meal
  once a month

sentinel®
spectrum® chews
(milbemycin oxime • lufenuron • praziquantel)

6 chewables

5.75 mg milbemycin oxime • 115 mg lufenuron • 57 mg praziquantel
CAUTION: Federal (USA) law restricts this drug to use by or on the order of a licensed veterinarian

PRINCIPAL DISPLAY PANEL - 6 Chewable Blister Pack Carton - 25.1-50lbs

MERCK
Animal Health

25.1-50lbs
FOR DOGS AND PUPPIES
SIX WEEKS OF AGE AND OLDER

Broad Spectrum
Parasiticide

- prevents heartworm
  disease
- prevents and controls
  flea populations
- treats and controls
  tapeworms, whipworms
  roundworms, hookworms
- give with a meal
  once a month

sentinel®
spectrum® chews
(milbemycin oxime • lufenuron • praziquantel)

6 chewables

11.5 mg milbemycin oxime • 230 mg lufenuron • 114 mg praziquantel
CAUTION: Federal (USA) law restricts this drug to use by or on the order of a licensed veterinarian

PRINCIPAL DISPLAY PANEL - 6 Chewable Blister Pack Carton - 50.1-100lbs

MERCK
Animal Health

50.1-100lbs
FOR DOGS AND PUPPIES
SIX WEEKS OF AGE AND OLDER

Broad Spectrum
Parasiticide

- prevents heartworm
  disease
- prevents and controls
  flea populations
- treats and controls
  tapeworms, whipworms
  roundworms, hookworms
- give with a meal
  once a month

sentinel®
spectrum® chews
(milbemycin oxime • lufenuron • praziquantel)

6 chewables

23 mg milbemycin oxime • 460 mg lufenuron • 228 mg praziquantel
CAUTION: Federal (USA) law restricts this drug to use by or on the order of a licensed veterinarian